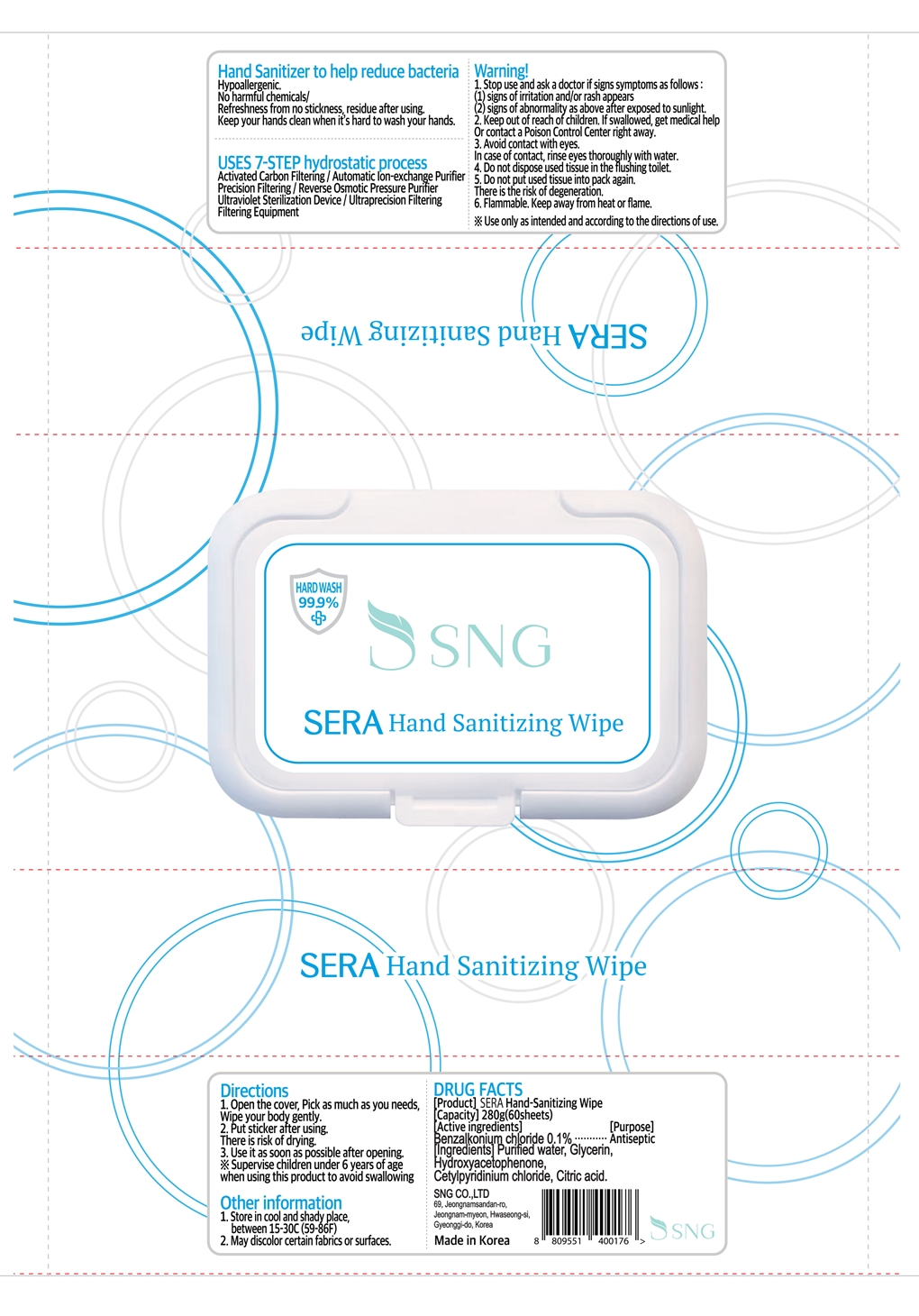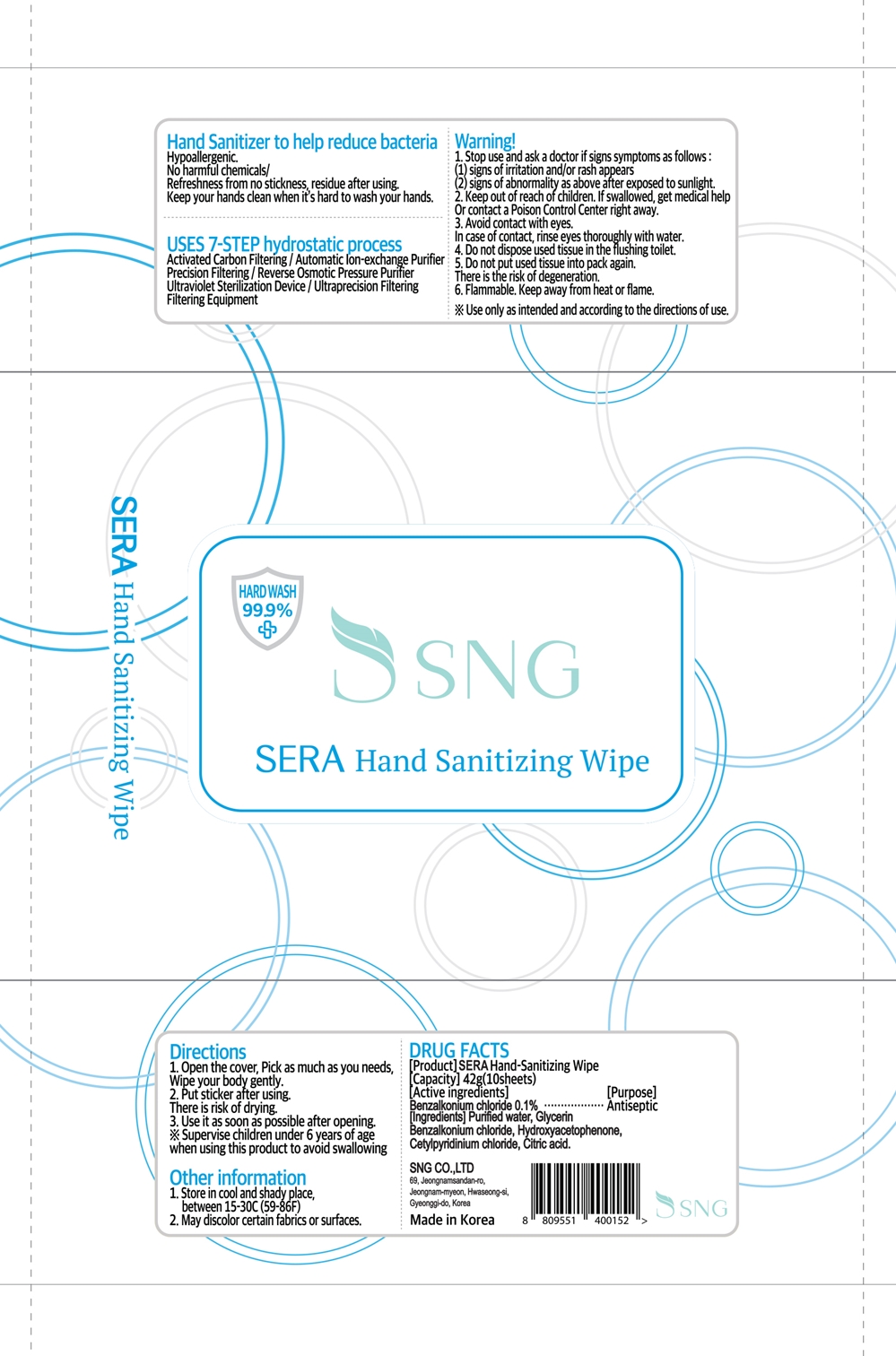 DRUG LABEL: SERA Hand-Sanitizing Wipe
NDC: 77822-201 | Form: LIQUID
Manufacturer: SNG CO., LTD
Category: otc | Type: HUMAN OTC DRUG LABEL
Date: 20221115

ACTIVE INGREDIENTS: BENZALKONIUM CHLORIDE 0.1 g/100 g
INACTIVE INGREDIENTS: WATER; CETYLPYRIDINIUM CHLORIDE; CITRIC ACID MONOHYDRATE; HYDROXYACETOPHENONE; GLYCERIN

Active ingredients

Benzalkonium chloride 0.1%

Purpose

Antiseptic

Inactive ingredient

Purified water, Glycerin, Hydroxyacetophenone, Cetylpyridinium chloride, Citric acid

Directions

1. Open the cover, Pick as much as you needs, Wipe your body gently.

2. Put sticker after using. There is risk of drying.

3. Use it as soon as possible after opening.

Supervise children under 6 years of age when using this product to avoid swallowing.

Other information

1. Store in cool and shady place, between 15-30C (59-86F)

2. May discolor certain fabrics or surfaces.

Hand Sanitizer to hlep reduce bacteria

Hypoallergenic.

No harmful chemicals/

Refreshness from no stickness, residue after using.

Keep your hands clean when it's hard to wash your hands.

Stop use and ask a docotr if signs symptoms as follows:

(1) signs of irritation and/or rash appears

(2) signs of abnormality as above after exposed to sunlight.

Keep out of reach of children.

If swallowed, get medical help or contact a Poison Control Center right away.

Avoid contact with eyes.

In case of contact, rinse eyes thoroughly with water.

Do not dispose used tissue in the flushing toilet.

Do not put used tissue into pack again.

There is the risk of degeneration.

Warning

Flammable. Keep away from heat or flame.

Use only as intended and according to the directions of use.